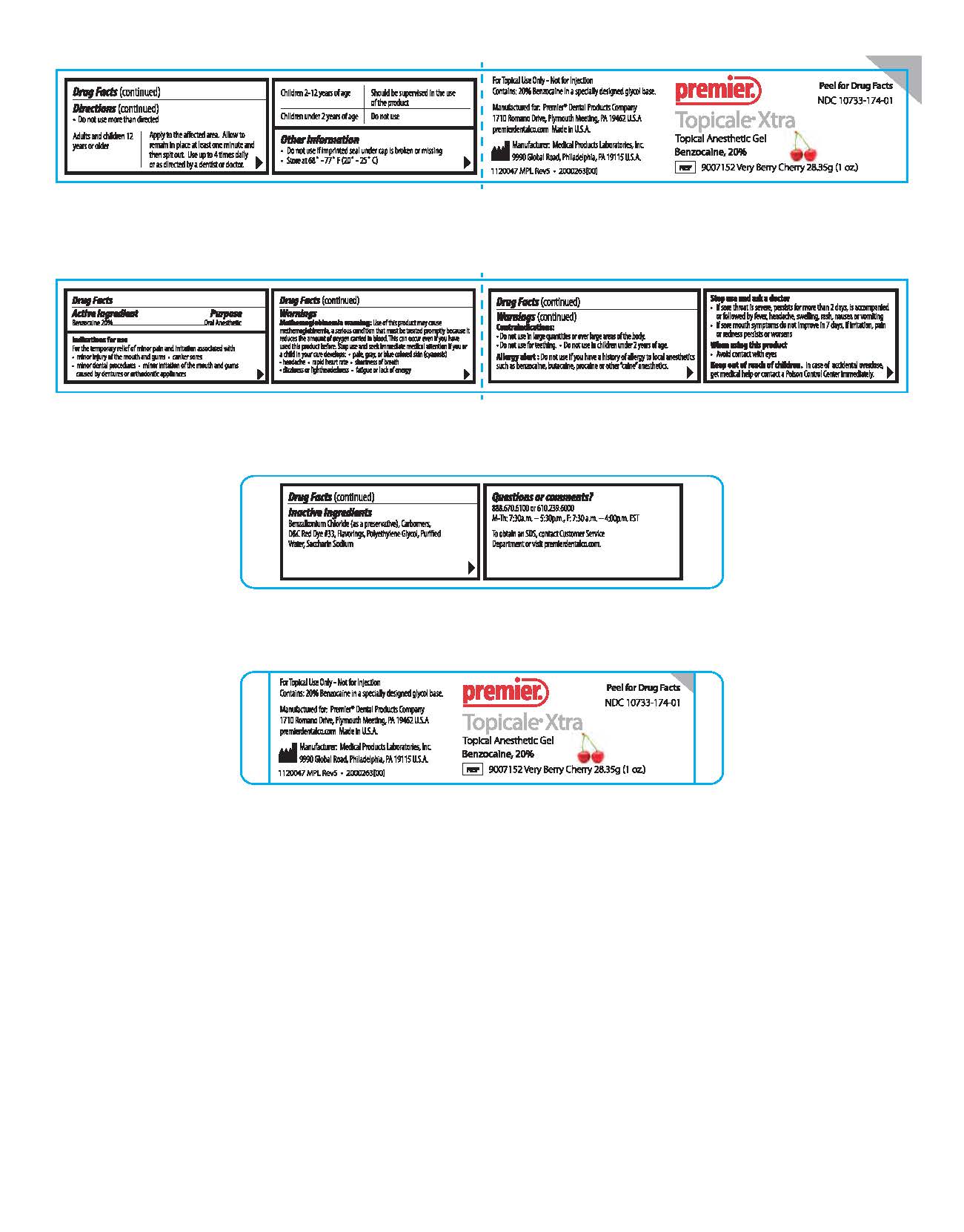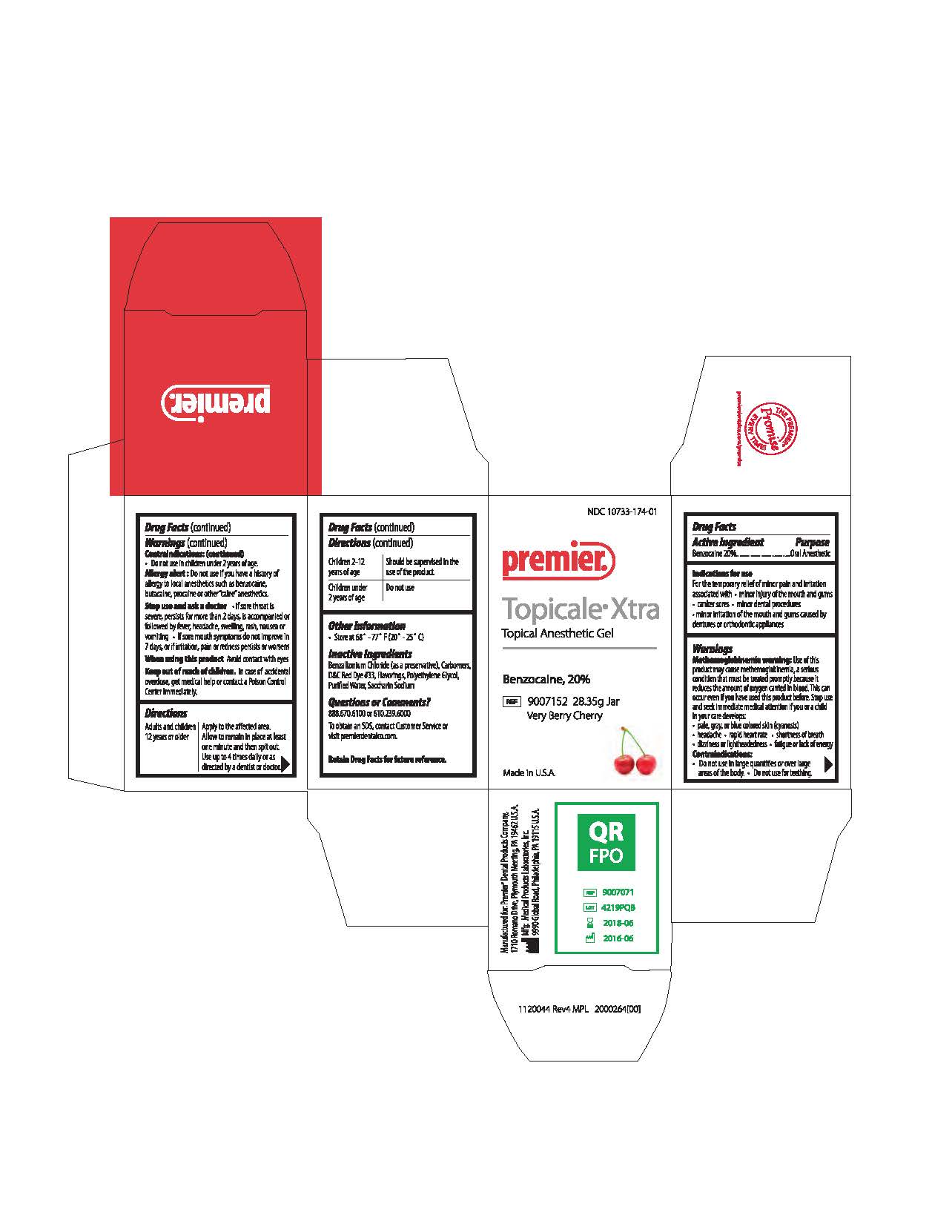 DRUG LABEL: Topicale Xtra
NDC: 10733-174 | Form: GEL
Manufacturer: Medical Products Laboratories,Inc.
Category: otc | Type: HUMAN OTC DRUG LABEL
Date: 20241216

ACTIVE INGREDIENTS: BENZOCAINE 200 mg/1 g
INACTIVE INGREDIENTS: POLYETHYLENE GLYCOL 400; WATER; D&C RED NO. 33; CARBOMER HOMOPOLYMER TYPE B (ALLYL PENTAERYTHRITOL OR ALLYL SUCROSE CROSSLINKED); BENZALKONIUM CHLORIDE; SACCHARIN SODIUM

Topicale Xtra Gel - Very Berry Cherry

ACTIVE INGREDIENT

Benzocaine 20%

PURPOSE

Oral Anesthetic

INDICATIONS AND USAGE

For the temporary relief of minor pain and irritation associated with minor injury of the mouth and gums, canker sores, minor dental procedures, minor irritation of the mouth and gums caused by dentures or orthodontic appliances

WARNINGS

Methemoglobinemia warning:

Use of this product may cause methemoglobinemia, a serious condition that must be treated promptly because it reduces the amount of oxygen carried in blood. This can occur even if you have used this product before. Stop use and seek immediate medical attention if you or a child in your care develops pale, grey or blue colored skin (cyanosis), headache, rapid heart rate, shortness of breath, dizziness or light headedness, fatigue or lack of energy.

Contraindications:

Do not use in large quantities or over large areas of body
Do not use for Teething
Do not use in children under 2 years of age

Allergy Alert:

Do not use if you have a history of allergy to local anesthetics such as benzocaine, butacaine, procaine or other "caine" anesthetics

When using this product

- Avoid contact with eyes

KEEP OUT OF REACH OF CHILDREN

In case of accidental overdose, get medical help or contact a Poison Control Centre immediately.

Stop use and ask a doctor

If sore throat is severe, persists for more than 2 days, is accompanied or followed by fever, headache, swelling, rash, nausea or vomiting
If sore mouth symptoms do not improve in 7 days, or if irritation, pain or redness persists or worsens

Do not use more than directed.

Adults and children 12 years or older - Apply to the affected area. Allow to remain in place at least one minute and the spit out. Use up to 4 times daily or as directed by a dentist or doctor.

Children 2-12 years of age - Should be supervised in the use of the product.

Children under 2 years of age - Do not use.

INACTIVE INGREDIENT

Benzalkonium Chloride (as a preservative), Carbomers, D&C Red Dye # 33, Flavorings, Polyethylene Glycol, Purified Water, Saccharin Sodium

INFORMATION FOR OWNERS/CAREGIVERS

Peel for Drug Facts

NDC 10733-174-01

Premier

Topicale Xtra

Topical Anesthetic Gel

Benzocaine, 20 %

REF 9007152 Very Berry Cherry 28.35g (1 o.z.)

For Topical Use only - Not for Injection

Contains: 20 % Benzocaine in a specially designed glycol base

Made in U.S.A.

premierdentalco.com

Manufactured for: Premier® Dental Products Company,
1710 Romano Drive, Plymouth Meeting, PA 19462 U.S.A.

Mfg: Medical Products Laboratories, Inc.
9990 Global Road Philadelphia, PA 19115 U.S.A.

1120047 MPL Rev5 . 2000263(00)

Questions or Comments?

888.670.6100 or 610.239.6000
M-Th: 7:30a.m. - 5:30p.m., F: 7:30a.m. - 4:00p.m. EST

To obtain an SDS, contact Customer Service Department or visit premierdentalco.com.